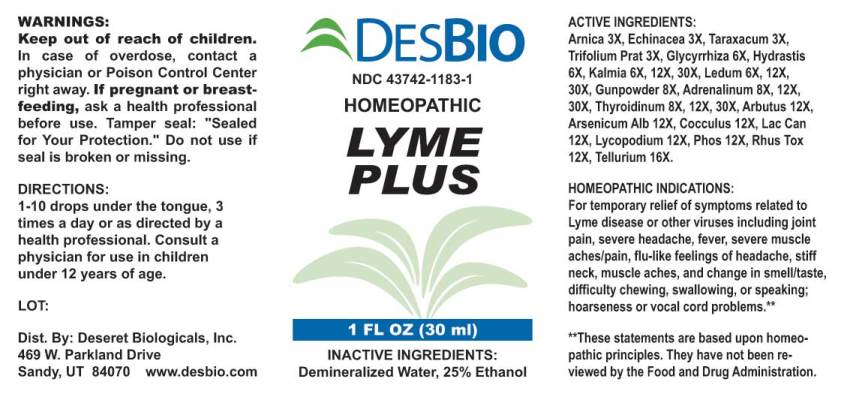 DRUG LABEL: Lyme Plus
NDC: 43742-1183 | Form: LIQUID
Manufacturer: Deseret Biologicals, Inc.
Category: homeopathic | Type: HUMAN OTC DRUG LABEL
Date: 20210811

ACTIVE INGREDIENTS: ARNICA MONTANA 3 [hp_X]/1 mL; ECHINACEA ANGUSTIFOLIA 3 [hp_X]/1 mL; TARAXACUM OFFICINALE 3 [hp_X]/1 mL; TRIFOLIUM PRATENSE FLOWER 3 [hp_X]/1 mL; GLYCYRRHIZA GLABRA 6 [hp_X]/1 mL; GOLDENSEAL 6 [hp_X]/1 mL; KALMIA LATIFOLIA LEAF 6 [hp_X]/1 mL; RHODODENDRON TOMENTOSUM LEAFY TWIG 6 [hp_X]/1 mL; ACTIVATED CHARCOAL 8 [hp_X]/1 mL; SULFUR 8 [hp_X]/1 mL; POTASSIUM NITRATE 8 [hp_X]/1 mL; EPINEPHRINE 8 [hp_X]/1 mL; SUS SCROFA THYROID 8 [hp_X]/1 mL; ARBUTUS ANDRACHNE LEAFY SHOOT 12 [hp_X]/1 mL; ARSENIC TRIOXIDE 12 [hp_X]/1 mL; ANAMIRTA COCCULUS SEED 12 [hp_X]/1 mL; CANIS LUPUS FAMILIARIS MILK 12 [hp_X]/1 mL; LYCOPODIUM CLAVATUM SPORE 12 [hp_X]/1 mL; PHOSPHORUS 12 [hp_X]/1 mL; TOXICODENDRON PUBESCENS LEAF 12 [hp_X]/1 mL; TELLURIUM 16 [hp_X]/1 mL
INACTIVE INGREDIENTS: WATER; ALCOHOL

Drug Facts:

ACTIVE INGREDIENTS:

Arnica Montana 3X, Echinacea (Angustifolia) 3X, Taraxacum Officinale 3X, Trifolium Pratense 3X, Glycyrrhiza Glabra 6X, Hydrastis Canadensis 6X, Kalmia Latifolia 6X, 12X 30X, Ledum Palustre 6X, 12X, 30X, Gunpowder 8X, Adrenalinum 8X, Thyroidinum (Suis) 8X, 12X, 30X, Arbutus Andrachne 12X, Arsenicum Album 12X, Cocculus Indicus 12X, Lac Caninum 12X, Lycopodium Clavatum 12X, Phosphorus 12X, Rhus Tox 12X, Tellurium Metallicum 16X.

HOMEOPATHIC INDICATIONS:

For temporary relief of symptoms related to Lyme disease or other viruses including joint pain, severe headache, fever, severe muscle aches/pain, flu-like feelings of headache, stiff neck, muscle aches, and change in smell/taste, difficulty chewing, swallowing, or speaking; hoarseness or vocal cord problems.**

**These statements are based upon traditional homeopathic principles. They have not been reviewed by the Food and Drug Administration.

WARNINGS:

Keep out of reach of children. In case of overdose, contact physician or a Poison Control Center right away.

If pregnant or breast-feeding, ask a health professional before use.

Tamper seal: "Sealed for Your Protection." Do not use if seal is broken or missing.

Keep out of reach of children. In case of overdose, contact physician or a Poison Control Center right away.

DIRECTIONS:

1-10 drops under the tongue, 3 times a day or as directed by a health professional. Consult a physician for use in children under 12 years of age.

HOMEOPATHIC INDICATIONS:

For temporary relief of symptoms related to Lyme disease or other viruses including joint pain, severe headache, fever, severe muscle aches/pain, flu-like feelings of headache, stiff neck, muscle aches, and change in smell/taste, difficulty chewing, swallowing, or speaking; hoarseness or vocal cord problems.**

**These statements are based upon traditional homeopathic principles. They have not been reviewed by the Food and Drug Administration.

INACTIVE INGREDIENTS:

Demineralized Water, 25% Ethanol

QUESTIONS:

Dist. By: Deseret Biologicals, Inc.
469 W. Parkland Drive
Sandy, UT 84070 www.desbio.com

PACKAGE LABEL DISPLAY:

DESBIO

NDC 43742-1183-1

HOMEOPATHIC

LYME

PLUS

1 FL OZ (30 ml)